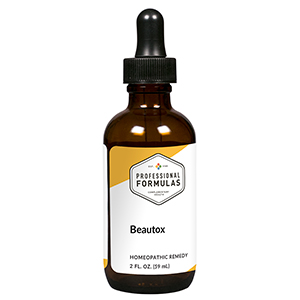 DRUG LABEL: Beautox
NDC: 63083-6007 | Form: LIQUID
Manufacturer: Professional Complementary Health Formulas
Category: homeopathic | Type: HUMAN OTC DRUG LABEL
Date: 20190815

ACTIVE INGREDIENTS: ECHINACEA ANGUSTIFOLIA WHOLE 2 [hp_X]/59 mL; BOS TAURUS BRAIN 6 [hp_X]/59 mL; CAMPHOR (NATURAL) 6 [hp_X]/59 mL; BEEF KIDNEY 6 [hp_X]/59 mL; BEEF LIVER 6 [hp_X]/59 mL; BEEF LUNG 6 [hp_X]/59 mL; BOS TAURUS PITUITARY GLAND, POSTERIOR 12 [hp_X]/59 mL; NITRIC ACID 12 [hp_X]/59 mL; PHOSPHORIC ACID 12 [hp_X]/59 mL; ACETYLDIGITOXIN 30 [hp_X]/59 mL
INACTIVE INGREDIENTS: ALCOHOL; WATER

X7

ACTIVE INGREDIENTS

Echinacea angustifolia 2X
Brain 6X
Camphora 6X
Kidney 6X
Liver 6X
Lung 6X
Hypophysis 12X
Nitricum acidum 12X
Phosphoricum acidum 12X
Cosmetologic toxins 30X, 60X, 100X

QUESTIONS

Professional Formulas

PO Box 2034 Lake Oswego, OR 97035

INDICATIONS

For the temporary relief of cough, shortness of breath, irritation of the eyes, nose, or throat, itchy, dry, or irritated skin, dizziness, or occasional headache due to sensitivity to or exposure to chemicals used in cosmetology.*

PURPOSE

*Claims based on traditional homeopathic practice, not accepted medical evidence. Not FDA evaluated.

WARNINGS

In case of overdose, get medical help or contact a poison control center right away.

Keep out of the reach of children.

PREGNANCY OR BREAST FEEDING

If pregnant or breastfeeding, ask a healthcare professional before use.

DIRECTIONS

Place drops under tongue 30 minutes before/after meals. Adults and children 12 years and over: Take 10 drops up to 3 times per day. Consult a physician for use in children under 12 years of age.

OTHER INFORMATION

Tamper resistant. If seal is broken, do not use. After opening, close container tightly and store at room temperature away from heat.

INACTIVE INGREDIENTS

20% ethanol, purified water.

LABEL

Est 1985

Professional Formulas

Complementary Health

Beautox

Homeopathic Remedy

2 FL. OZ. (59 mL)